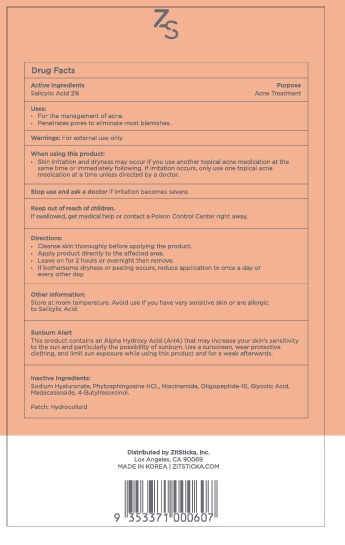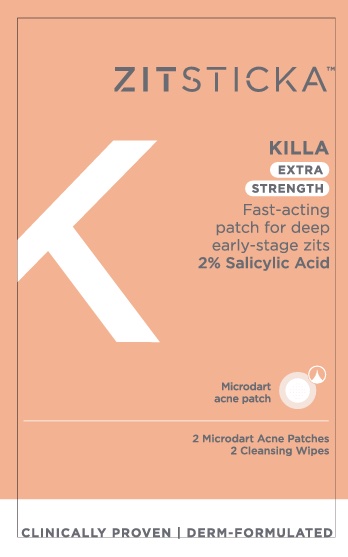 DRUG LABEL: Killa Extra Strength 2 pack
NDC: 81746-526 | Form: PATCH
Manufacturer: ZitSticka, Inc.
Category: otc | Type: HUMAN OTC DRUG LABEL
Date: 20251001

ACTIVE INGREDIENTS: SALICYLIC ACID 0.0125 mg/0.6216 mg
INACTIVE INGREDIENTS: 4-BUTYLRESORCINOL; PHYTOSPHINGOSINE HYDROCHLORIDE; GLYCOLIC ACID; NIACINAMIDE; OLIGOPEPTIDE-10; HYALURONATE SODIUM; MADECASSOSIDE

Killa Extra Strength 2 pack

Ask a doctor if irritation become severe.

Keep out of reach of children. If swallowed, get medical help or contact a posion Control Center right away.

Uses:

- For the management of acne.
- Penetrates pores to eliminate most blemishes.

WARNINGS AND PRECAUTIONS

For External Use only